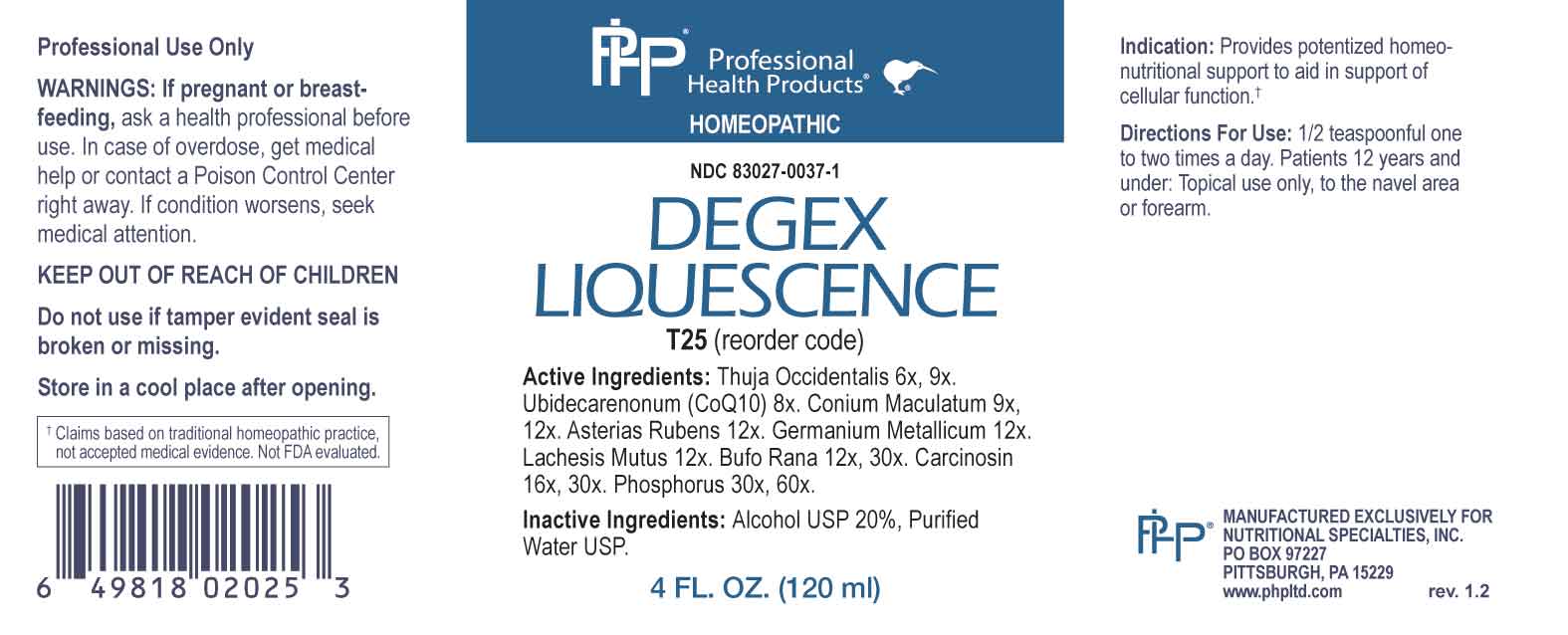 DRUG LABEL: Degex Liquescence
NDC: 83027-0037 | Form: LIQUID
Manufacturer: Nutritional Specialties, Inc.
Category: homeopathic | Type: HUMAN OTC DRUG LABEL
Date: 20250515

ACTIVE INGREDIENTS: THUJA OCCIDENTALIS LEAFY TWIG 6 [hp_X]/1 mL; UBIDECARENONE 8 [hp_X]/1 mL; CONIUM MACULATUM FLOWERING TOP 9 [hp_X]/1 mL; ASTERIAS RUBENS 12 [hp_X]/1 mL; GERMANIUM 12 [hp_X]/1 mL; LACHESIS MUTA VENOM 12 [hp_X]/1 mL; BUFO BUFO CUTANEOUS GLAND 12 [hp_X]/1 mL; HUMAN BREAST TUMOR CELL 16 [hp_X]/1 mL; PHOSPHORUS 30 [hp_X]/1 mL
INACTIVE INGREDIENTS: WATER; ALCOHOL

DRUG FACTS:

ACTIVE INGREDIENTS:

Thuja Occidentalis 6X, 9X, Ubidecarenonum (CoQ10) 8X, Conium Maculatum 9X, 12X, Asterias Rubens 12X, Germanium Metallicum 12X, Lachesis Mutus 12X, Bufo Rana 12X, 30X, Carcinosin 16X, 30X, Phosphorus 30X, 60X.

PURPOSE:

Provides potentized homeo-nutritional support to aid in support of cellular function.†

†Claims based on traditional homeopathic practice, not accepted medical evidence. Not FDA evaluated.

WARNINGS:

Professional Use Only

If pregnant or breast-feeding, ask a health professional before use.

In case of overdose, get medical help or contact a Poison Control Center right away.

If condition worsens, seek medical attention.

KEEP OUT OF REACH OF CHILDREN

Do not use if tamper evident seal is broken or missing.

Store in a cool place after opening

KEEP OUT OF REACH OF CHILDREN:

In case of overdose, get medical help or contact a Poison Control Center right away.

DIRECTIONS:

1/2 teaspoonful one to two times a day. Patients 12 years and under: Topical use only, to the navel area or forearm.

INDICATIONS:

Provides potentized homeo-nutritional support to aid in support of cellular function.†

†Claims based on traditional homeopathic practice, not accepted medical evidence. Not FDA evaluated.

INACTIVE INGREDIENTS:

Alcohol USP 20%, Purified Water USP.

QUESTIONS:

MANUFACTURED EXCLUSIVELY FOR

NUTRITIONAL SPECIALTIES, INC.

PO BOX 97227

PITTSBURG, PA 15229

www.phpltd.com

PACKAGE LABEL DISPLAY:

Professional

Health Products

HOMEOPATHIC

NDC 83027-0037-1

DEGEX

LIQUESCENCE

4 FL. OZ (120 ml)